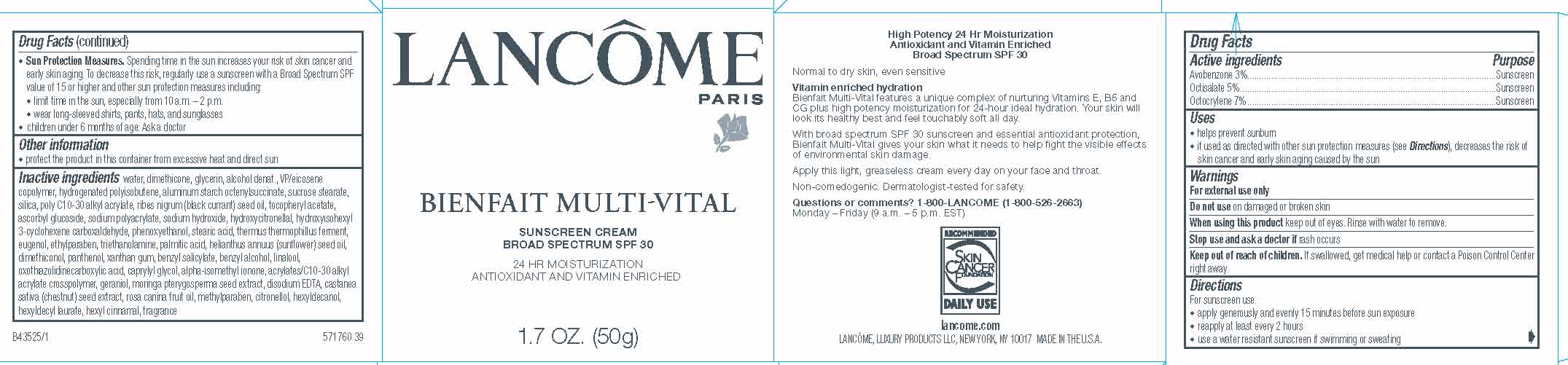 DRUG LABEL: Lancome Paris Bienfait MultiVital Broad Spectrum SPF 30 Sunscreen
NDC: 49967-456 | Form: CREAM
Manufacturer: L'Oreal USA Products Inc
Category: otc | Type: HUMAN OTC DRUG LABEL
Date: 20231223

ACTIVE INGREDIENTS: AVOBENZONE 30 mg/1 g; OCTISALATE 50 mg/1 g; OCTOCRYLENE 70 mg/1 g
INACTIVE INGREDIENTS: WATER; DIMETHICONE; GLYCERIN

Drug Facts

Active ingredients

Avobenzone 3%

Octisalate 5%

Octocrylene 7%

Purpose

Sunscreen

Uses

- helps prevent sunburn
- if used as directed with other sun protection measures (see Directions), decreases the risk of skin cancer and early skin aging caused by the sun

Warnings

For external use only

Do not use

on damaged or broken skin

When using this product

keep out of eyes. Rinse with water to remove.

Stop use and ask a doctor if

rash occurs

Keep out of reach of children.

If swallowed, get medical help or contact a Poison Control Center right away.

Directions

For sunscreen use:

● apply generously and evenly 15 minutes before sun exposure

● reapply at least every 2 hours

● use a water resistant sunscreen if swimming or sweating

● Sun Protection Measures. Spending time in the sun increases your risk of skin cancer and early skin aging. To decrease this risk, regularly use a sunscreen with a Broad Spectrum SPF value of 15 or higher and other sun protection measures including:

● limit time in the sun, especially from 10 a.m. – 2 p.m.

● wear long-sleeved shirts, pants, hats, and sunglasses

● children under 6 months of age: Ask a doctor

Other information

protect the product in this container from excessive heat and direct sun

Inactive ingredients

water, dimethicone, glycerin, alcohol denat., VP/eicosene copolymer, hydrogenated polyisobutene, aluminum starch octenylsuccinate, sucrose stearate, silica, poly C10-30 alkyl acrylate, ribes nigrum (black currant) seed oil, tocopheryl acetate, ascorbyl glucoside, sodium polyacrylate, sodium hydroxide, hydroxycitronellal, hydroxyisohexyl 3-cyclohexene carboxaldehyde, phenoxyethanol, stearic acid, thermus thermophillus ferment, eugenol, ethylparaben, triethanolamine, palmitic acid helianthus annuus (sunflower) seed oil, dimethiconol, panthenol, xanthan gum, benzyl salicylate, benzyl alcohol, linalool, oxothiazolidinecarboxylic acid, caprylyl glycol, alpha-isomethyl ionone, acrylates/C10-30 alkyl acrylate crosspolyer, geraniol, moringa pterygosperma seed extract, disodium EDTA, castanea sativa (chestnut) seed exteract, rosa canina fruit oil, methylparaben, citronellol, hexyldecanol, hexyldecyl laurate, hexyl cinnamal, fragrance

Questions or comments?

1-800-LANCOME (1-800-526-2663) Monday - Friday(9 a.m. - 5 p.m. EST)